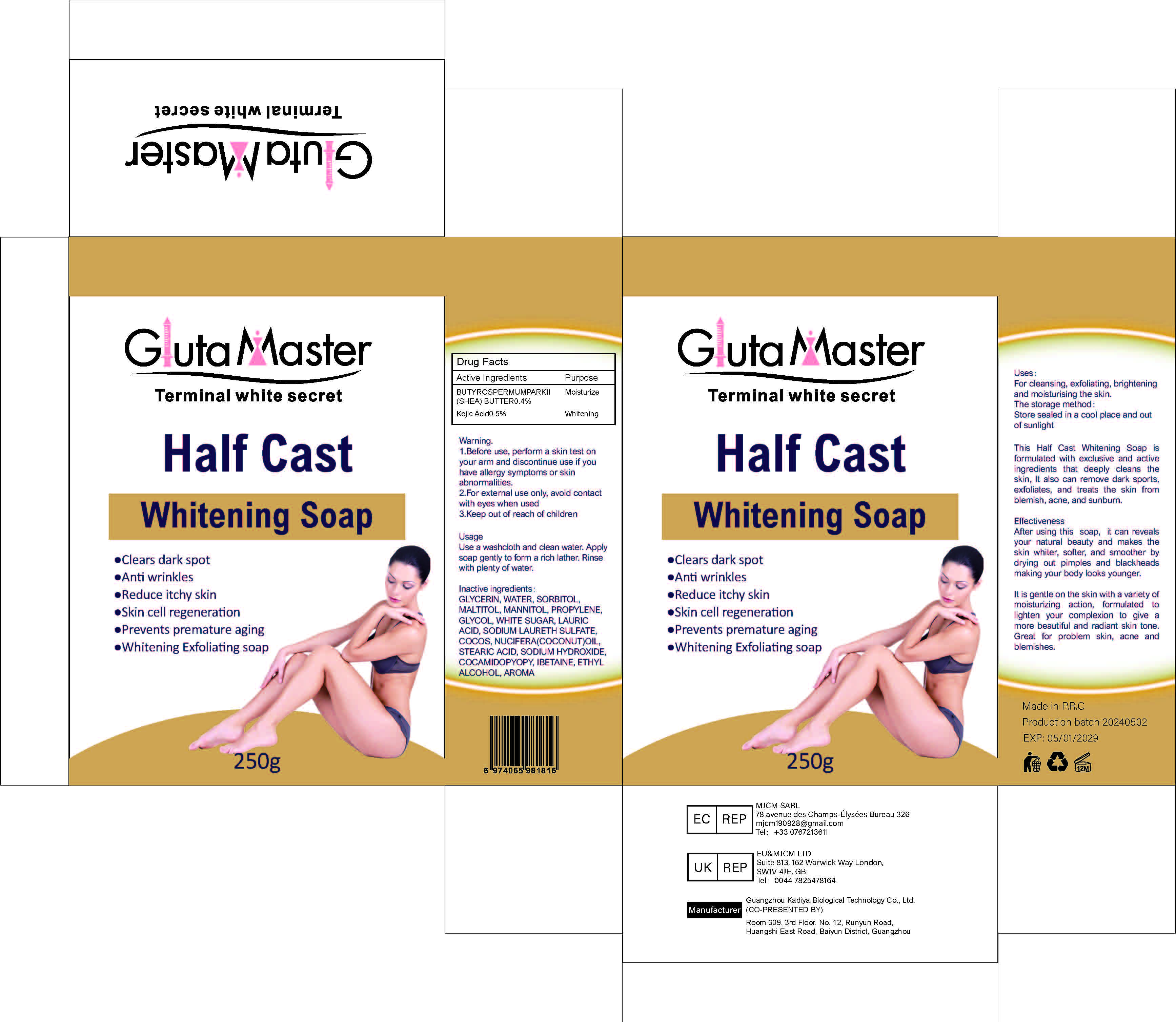 DRUG LABEL: Whitening ExfoliatingSoap
NDC: 84423-012 | Form: SOAP
Manufacturer: Guangzhou Kadiya Biotechnology Co., Ltd.
Category: otc | Type: HUMAN OTC DRUG LABEL
Date: 20240708

ACTIVE INGREDIENTS: BUTYROSPERMUM PARKII (SHEA) BUTTER UNSAPONIFIABLES 1 mg/250 mL; KOJIC ACID 1.25 mg/250 mL
INACTIVE INGREDIENTS: MANNITOL; WATER; PROPYLENE GLYCOL; LAURIC ACID; SODIUM HYDROXIDE; ALCOHOL; COCOS NUCIFERA WHOLE; STEARIC ACID; COCO/OLEAMIDOPROPYL BETAINE; MALTITOL; SORBITOL; SODIUM LAURETH SULFATE; GLYCERIN; SUCROSE

Uses：
For cleansing, exfoliating, brightening and moisturising the skin.

INACTIVE INGREDIENT

GLYCERIN、WATER、SORBITOL、MALTITOL、MANNITOL、PROPYLENE、GLYCOL、WHITE SUGAR、LAURIC ACID、SODIUM LAURETH SULFATE、COCOS、NUCIFERA(COCONUT)OIL、STEARIC ACID 、SODIUM HYDROXIDE、COCAMIDOPYOPY、IBETAINE、ETHYL ALCOHOL、OLEAEUROPAEA(OLIVE)FRUIT OLL、BUTYROSPERMUMPARKII(SHEA)BUTTER、AROMA

Warning.
1.Before use, perform a skin test on your arm and discontinue use if you have allergy symptoms or skin abnormalities.
2、For external use only, avoid contact with eyes when used
3、Keep out of reach of children

Uses：
For cleansing, exfoliating, brightening and moisturising the skin.

KEEP OUT OF REACH OF CHILDREN SECTION

DOSAGE AND ADMINISTRATION

Use a washcloth and clean water.
Apply soap gently to form a rich lather.
Rinse with plenty of water.

Active Ingredients
BUTYROSPERMUMPARKII(SHEA)BUTTER 0.4%
Kojic Acid 0.5%

Uses：
For cleansing, exfoliating, brightening and moisturising the skin.
Indications: For skin whitening cleansing exfoliation
The storage method：
Store sealed in a cool place and out of sunlight

Warning.
1.Before use, perform a skin test on your arm and discontinue use if you have allergy symptoms or skin abnormalities.
2、For external use only, avoid contact with eyes when used
3、Keep out of reach of children

Inactive ingredients：
GLYCERIN、WATER、SORBITOL、MALTITOL、MANNITOL、PROPYLENE、GLYCOL、WHITE SUGAR、LAURIC ACID、SODIUM LAURETH SULFATE、COCOS、NUCIFERA(COCONUT)OIL、STEARIC ACID 、SODIUM HYDROXIDE、COCAMIDOPYOPY、IBETAINE、ETHYL ALCOHOL、OLEAEUROPAEA(OLIVE)FRUIT OLL、BUTYROSPERMUMPARKII(SHEA)BUTTER、AROMA